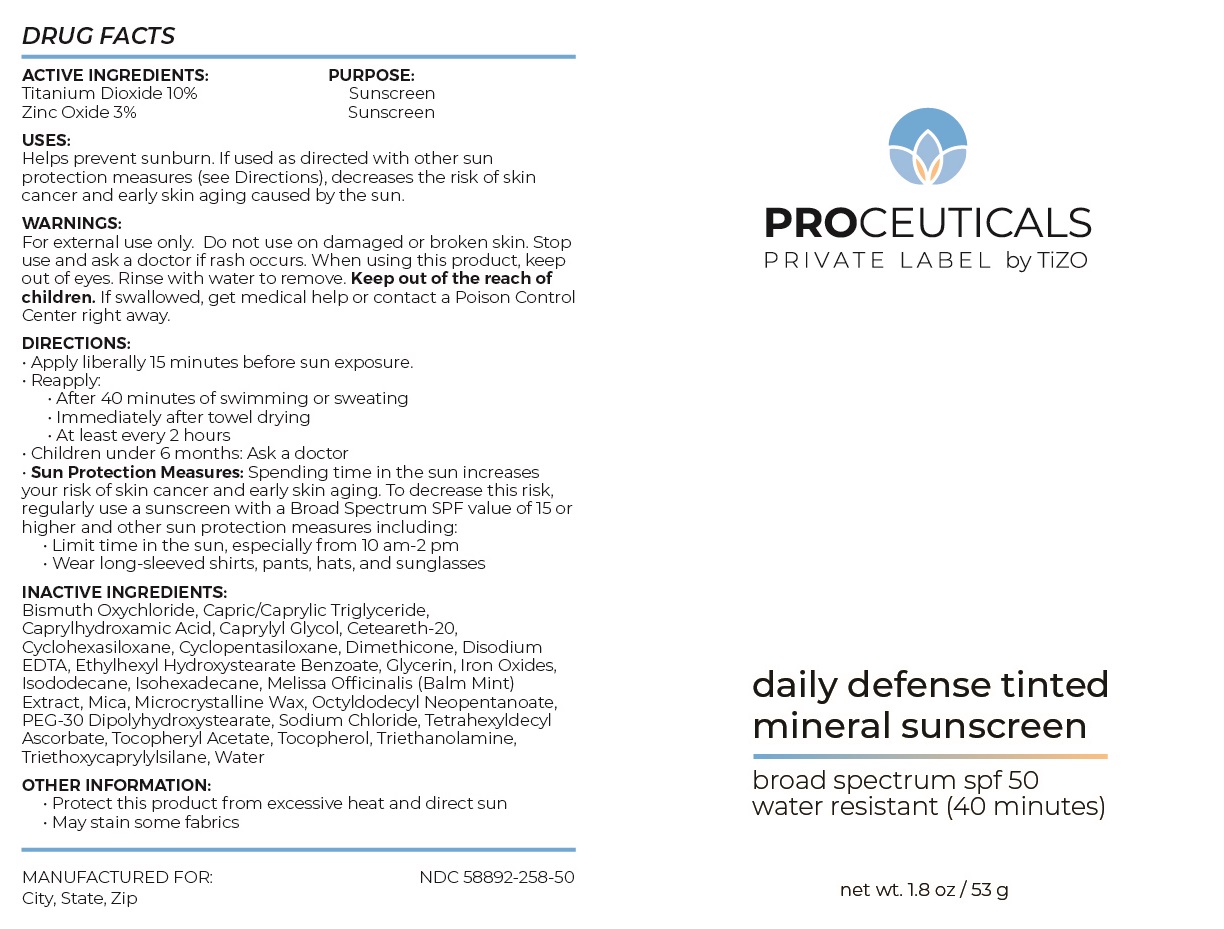 DRUG LABEL: PROCEUTICALS PRIVATE LABEL by TiZO daily defense tinted mineral sunscreen
NDC: 58892-258 | Form: CREAM
Manufacturer: Fallien Cosmeceuticals, LTD
Category: otc | Type: HUMAN OTC DRUG LABEL
Date: 20240708

ACTIVE INGREDIENTS: ZINC OXIDE 30 mg/1 g; TITANIUM DIOXIDE 100 mg/1 g
INACTIVE INGREDIENTS: FERRIC OXIDE YELLOW; BISMUTH OXYCHLORIDE; CAPRYLHYDROXAMIC ACID; CAPRYLYL GLYCOL; ETHYLHEXYL HYDROXYSTEARATE BENZOATE; CYCLOMETHICONE 6; CYCLOMETHICONE 5; MELISSA OFFICINALIS WHOLE; WATER; POLYOXYL 20 CETOSTEARYL ETHER; GLYCERIN; ISOHEXADECANE; MICROCRYSTALLINE WAX; SODIUM CHLORIDE; TETRAHEXYLDECYL ASCORBATE; FERRIC OXIDE RED; OCTYLDODECYL NEOPENTANOATE; .ALPHA.-TOCOPHEROL ACETATE; EDETATE DISODIUM ANHYDROUS; MEDIUM-CHAIN TRIGLYCERIDES; DIMETHICONE; FERROSOFERRIC OXIDE; PEG-30 DIPOLYHYDROXYSTEARATE (4000 MW); TRIETHOXYCAPRYLYLSILANE; ISODODECANE; MICA; TOCOPHEROL; TROLAMINE

ACTIVE INGREDIENTS:
Titanium Dioxide 10%
Zinc Oxide 3%

PURPOSE:Sunscreen

DIRECTIONS:
• Apply liberally 15 minutes before sun exposure.
• Reapply:
• After 40 minutes of swimming or sweating
• Immediately after towel drying
• At least every 2 hours
• Children under 6 months: Ask a doctor
• Sun Protection Measures: Spending time in the sun increases
your risk of skin cancer and early skin aging. To decrease this risk,
regularly use a sunscreen with a Broad Spectrum SPF value of 15 or
higher and other sun protection measures including:
• Limit time in the sun, especially from 10 am-2 pm
• Wear long-sleeved shirts, pants, hats, and sunglasses

INACTIVE INGREDIENTS:
Bismuth Oxychloride, Capric/Caprylic Triglyceride,
Caprylhydroxamic Acid, Caprylyl Glycol, Ceteareth-20,
Cyclohexasiloxane, Cyclopentasiloxane, Dimethicone, Disodium
EDTA, Ethylhexyl Hydroxystearate Benzoate, Glycerin, Iron Oxides,
Isododecane, Isohexadecane, Melissa Officinalis (Balm Mint)
Extract, Mica, Microcrystalline Wax, Octyldodecyl Neopentanoate,
PEG-30 Dipolyhydroxystearate, Sodium Chloride, Tetrahexyldecyl
Ascorbate, Tocopheryl Acetate, Tocopherol, Triethanolamine,
Triethoxycaprylylsilane, Water

OTHER INFORMATION:
• Protect this product from excessive heat and direct sun
• May stain some fabrics

WARNINGS:
For external use only. Do not use on damaged or broken skin. Stop
use and ask a doctor if rash occurs. When using this product, keep
out of eyes. Rinse with water to remove. Keep out of the reach of
children. If swallowed, get medical help or contact a Poison Control
Center right away.

Keep out of the reach of
children.

DOSAGE AND ADMINISTRATION

Helps prevent sunburn. If used as directed with other sun
protection measures (see Directions), decreases the risk of skin
cancer and early skin aging caused by the sun.

Apply liberally 15 minutes before sun exposure.

Principal Display Panel – 53 g Bottle Label

Proceuticals

PRIVATE LABEL by TiZO

daily defense tinted
mineral sunscreen

broad spectrum spf 50
water resistant (40 minutes)

net wt. 1.8 oz / 53 g

Graphic-Untitled